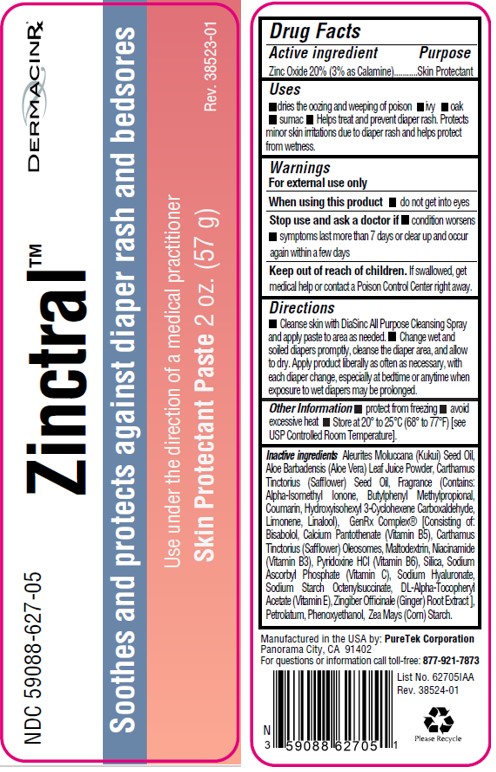 DRUG LABEL: Zinctral
NDC: 59088-627 | Form: PASTE
Manufacturer: PureTek Corporation
Category: otc | Type: HUMAN OTC DRUG LABEL
Date: 20240415

ACTIVE INGREDIENTS: ZINC OXIDE 20 g/100 g
INACTIVE INGREDIENTS: STARCH, CORN; ALUMINUM STARCH OCTENYLSUCCINATE; LEVOMENOL; KUKUI NUT OIL; ALOE VERA LEAF; CALCIUM PANTOTHENATE; CARTHAMUS TINCTORIUS (SAFFLOWER) OLEOSOMES; MALTODEXTRIN; NIACINAMIDE; PETROLATUM; PHENOXYETHANOL; PYRIDOXINE HYDROCHLORIDE; SILICON DIOXIDE; SODIUM ASCORBYL PHOSPHATE; HYALURONATE SODIUM; GINGER; .ALPHA.-TOCOPHEROL ACETATE, DL-; SAFFLOWER OIL

Zinctral
Zinc Oxide 20% (3% as Calamine)

Active ingredient

Zinc Oxide 20.0%

(3.0% as Calamine)

Purpose

Skin Protectant

Uses

- dries the oozing and weeping of poison:
- ivy
- oak
- sumac
- Helps treat and prevent diaper rash. Protects minor skin irritations due to diaper rash and helps protect from wetness.

Warnings

For external use only

When using this product

- do not get into eyes

Stop use and ask a doctor if

- condition worsens
- symptoms last more than 7 days or clear up and occur again within a few days

Keep out of reach of childern.

If swallowed, get medical help or contact a Poison Control Center right away.

Directions

- Cleanse skin with DiaSinc All Purpose Cleansing Spray and apply paste to area as needed.
- Change wet and soiled diapers promptly, cleanse the diaper area, and allow to dry. Apply product liberally as often as necessary, with each diaper change, especially at bedtime or anytime when exposure to wet diapers may be prolonged.

Other information

- protect from freezing
- avoid excessive heat
- Store at 20° to 25°C (68° to 77°F) [see USP Controlled Room Temperature].

Inactive ingredients:

Aleurites Moluccana (Kukui) Seed Oil, Aloe Barbadensis (Aloe Vera) Leaf Juice Powder, Carthamus Tinctorius (Safflower) Seed Oil, Fragrance (Contains: Alpha-Isomethyl Ionone, Butylphenyl Methylpropional, Coumarin, Hydroxyisohexyl 3-Cyclohexene Carboxaldehyde, Limonene, Linalool), GenRx Complex® [Consisting of: Bisabolol, Calcium Pantothenate (Vitamin B5), Carthamus Tinctorius (Safflower) Oleosomes, Maltodextrin, Niacinamide (Vitamin B3), Pyridoxine HCl (Vitamin B6), Silica, Sodium Ascorbyl Phosphate (Vitamin C), Sodium Hyaluronate, Sodium Starch Octenylsuccinate, DL-Alpha-Tocopheryl Acetate (Vitamin E), Zingiber Officinale (Ginger) Root Extract ], Petrolatum, Phenoxyethanol, Zea Mays (Corn) Starch.

Zinctral™

Manufactured in the USA by:

PureTek Corporation
Panorama City, CA 91402
For questions or information call toll-free: 877-921-7873